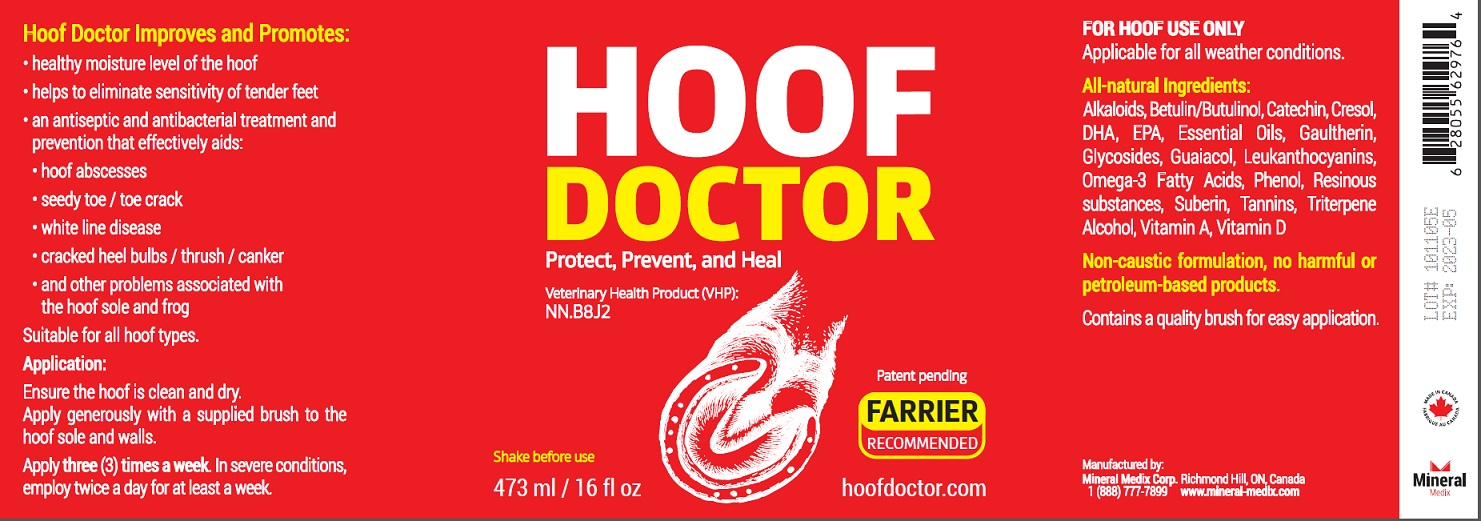 DRUG LABEL: Hoof Doctor
NDC: 86128-001 | Form: OINTMENT
Manufacturer: Mineral Medix Corp.
Category: animal | Type: OTC ANIMAL DRUG LABEL
Date: 20200722

ACTIVE INGREDIENTS: OMEGA-3 FATTY ACIDS 95 g/100 mL; BETULA PUBESCENS BARK 5 g/100 mL

Active Ingredient

Omega-3 Fatty Acid, Betula Pubescens Bark

Purpose

Topical hoof ointment to protect, prevent and heal most common hoof related issues

Use

To protect, prevent and heal most common hoof related issues.
Hoof Doctor Improves and Promotes:
• healthy moisture level of the hoof
• helps to eliminate sensitivity of tender feet
• an antiseptic and antibacterial treatment and prevention that effectively aids:
hoof abscesses, seedy toe / toe crack, white line disease, cracked heel bulbs / thrush / canker, and other problems associated with the hoof sole and frog.
Suitable for all hoof types.

Warnings

For hoof use only.

Application

Ensure the hoof is clean and dry. Apply generously with a supplied brush to the hoof sole and walls. Apply three (3) times a week. In severe conditions, employ twice a day for at least a week.